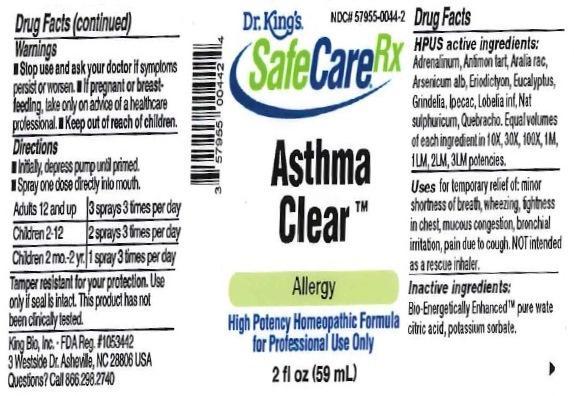 DRUG LABEL: Asthma Clear
NDC: 57955-0044 | Form: LIQUID
Manufacturer: King Bio Inc.
Category: homeopathic | Type: HUMAN OTC DRUG LABEL
Date: 20170131

ACTIVE INGREDIENTS: EPINEPHRINE 10 [hp_X]/59 mL; ANTIMONY POTASSIUM TARTRATE 10 [hp_X]/59 mL; ARALIA RACEMOSA ROOT 10 [hp_X]/59 mL; ARSENIC TRIOXIDE 10 [hp_X]/59 mL; ERIODICTYON CALIFORNICUM LEAF 10 [hp_X]/59 mL; EUCALYPTUS GLOBULUS LEAF 10 [hp_X]/59 mL; GRINDELIA SQUARROSA WHOLE 10 [hp_X]/59 mL; IPECAC 10 [hp_X]/59 mL; LOBELIA INFLATA 10 [hp_X]/59 mL; SODIUM SULFATE 10 [hp_X]/59 mL; ASPIDOSPERMA QUEBRACHO-BLANCO BARK 10 [hp_X]/59 mL
INACTIVE INGREDIENTS: WATER; ANHYDROUS CITRIC ACID; POTASSIUM SORBATE

Asthma Clear™

ACTIVE INGREDIENT

Drug Facts__________________________________________________________________________________________________________

HPUS active ingredients: Adrenalinum, Antimonium tartaricum, Aralia racemosa, Arsenicum album, Eriodictyon californicum, Eucalyptus globulus, Grindelia, Ipecacuanha, Lobelia inflata, Natrum sulphuricum, Quebracho. Equal volumes of each ingredient in 10X, 30X, 100X, 1M, 1LM, 2LM, 3LM potencies.

INDICATIONS AND USAGE

Uses for temporary relief of: minor shortness of breath, wheezing, tightness in chest, mucous congestion, bronchial irritation, pain due to cough, NOT intended as a rescue inhaler.

Inactive Ingredients:

Bio-Energetically Enhanced™ pure water, citric acid and potassium sorbate.

Warnings

- Stop use and ask your doctor if symptoms persist or worsen.
- If pregnant or breast-feeding, ask a healthcare professional before use.

- Keep out of reach of children.

Directions

- Initially, depress pump until primed.
- Spray one dose directly into mouth.
- Adults 12 and up: 3 sprays 3 times per day.
- Children 2-12: 2 sprays 3 times per day.
- Children 2 mo.-2 yr. 1 spray 3 times per day.

OTHER SAFETY INFORMATION

Tamper resistant for your protection. Use only if safety seal is intact. This product has not been clinically tested.

PURPOSE

Uses for temporary relief of: minor shortness of breath, wheezing, tightness in chest, mucous congestion, bronchial irritation, pain due to cough, NOT intended as a rescue inhaler.